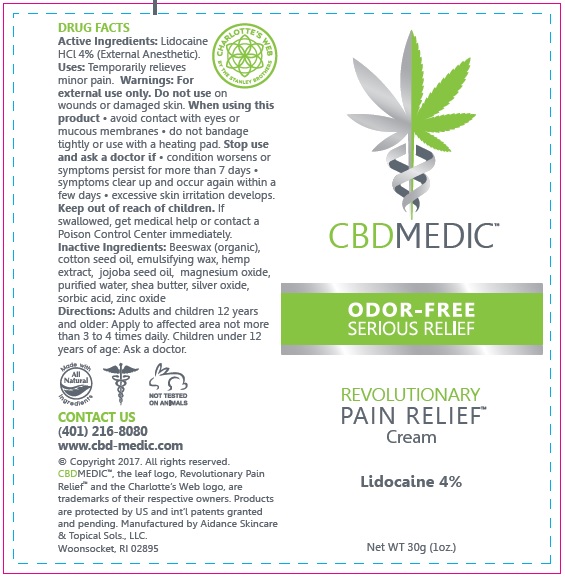 DRUG LABEL: CBD Medic - Odor-Free Serious Relief
NDC: 24909-721 | Form: CREAM
Manufacturer: Aidance Skincare & Topical Solutions, LLC
Category: otc | Type: HUMAN OTC DRUG LABEL
Date: 20170403

ACTIVE INGREDIENTS: LIDOCAINE HYDROCHLORIDE 4 g/100 g
INACTIVE INGREDIENTS: CETOSTEARYL ALCOHOL; COTTONSEED OIL; HEMP; JOJOBA OIL; MAGNESIUM OXIDE; POLYSORBATE 60; SHEA BUTTER; SILVER OXIDE; SORBIC ACID; WATER; WHITE WAX; ZINC OXIDE

Drug Facts

Active Ingredient

Lidocaine HCL 4%

Purpose

Lidocaine HCL - External Analgesic

Uses

Temporarily relieves minor pain.

Warnings

For external use only. Do not use on wounds or damaged skin. When using this product - avoid contact with eyes or mucous membranes - do not bandage tightly or use with heating pad. Stop use and ask a doctor if - condition worsens or symptoms persist for more than 7 days - symptoms clear up and occur again within a few days - excessive skin irritation develops.

Keep out of reach of children.

If swallowed, get medical help or contact a Poison Control Center immediately.

Directions

Adults and children 12 years of age and older: Apply to affected area not more than 3 to 4 times daily. Children under 12 years of age: Ask a doctor.

Inactive Ingredients

Beeswax (organic), cotton seed oil, emulsifying wax, hemp extract, jojoba seed oil, magnesium oxide, purified water, shea butter, silver oxide, sorbic acid, zinc oxide.

PRINCIPAL DISPLAY PANEL - 30g Size

CBDMEDIC

ODOR-FREE
SERIOUS RELIEF
Revolutionary Pain Relief
Lidocaine 4%

Net WT 30g (1oz.)